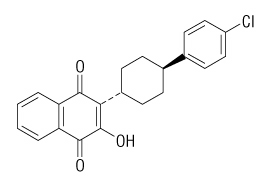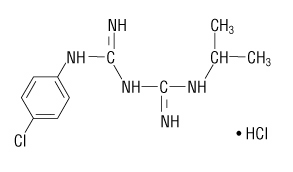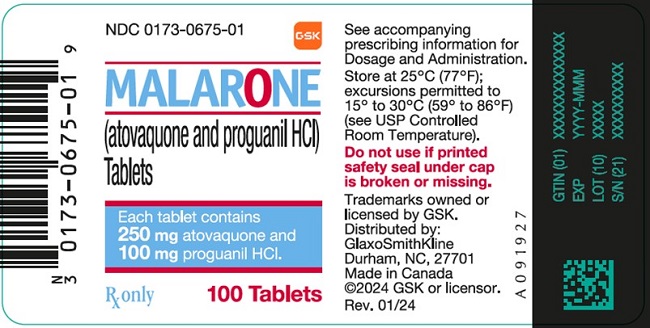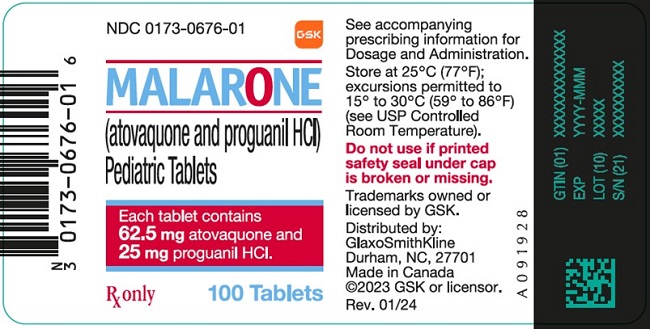 DRUG LABEL: MALARONE
NDC: 0173-0675 | Form: TABLET, FILM COATED
Manufacturer: GlaxoSmithKline LLC
Category: prescription | Type: HUMAN PRESCRIPTION DRUG LABEL
Date: 20231114

ACTIVE INGREDIENTS: ATOVAQUONE 250 mg/1 1; PROGUANIL HYDROCHLORIDE 100 mg/1 1
INACTIVE INGREDIENTS: LOW-SUBSTITUTED HYDROXYPROPYL CELLULOSE, UNSPECIFIED; MAGNESIUM STEARATE; MICROCRYSTALLINE CELLULOSE; POLOXAMER 188; POVIDONE K30; SODIUM STARCH GLYCOLATE TYPE A POTATO; HYPROMELLOSE, UNSPECIFIED; POLYETHYLENE GLYCOL 400; POLYETHYLENE GLYCOL 8000; FERRIC OXIDE RED; TITANIUM DIOXIDE

HIGHLIGHTS OF PRESCRIBING INFORMATION

These highlights do not include all the information needed to use MALARONE safely and effectively. See full prescribing information for MALARONE.
MALARONE (atovaquone and proguanil hydrochloride) tablets
MALARONE (atovaquone and proguanil hydrochloride) pediatric tablets
Initial U.S. Approval: 2000

1 INDICATIONS AND USAGE

MALARONE is an antimalarial indicated for:

- prophylaxis of Plasmodium falciparum malaria, including in areas where chloroquine resistance has been reported. (1.1)
- treatment of acute, uncomplicated P. falciparum malaria. (1.2)

2 DOSAGE AND ADMINISTRATION

- MALARONE should be taken with food or a milky drink.

Prophylaxis (2.1):

- Start prophylaxis 1 or 2 days before entering a malaria‑endemic area and continue daily during the stay and for 7 days after return.
- Adults: One adult strength tablet per day.
- Pediatric Patients: Dosage based on body weight (see Table 1).

Treatment (2.2):

- Adults: Four adult strength tablets as a single daily dose for 3 days.
- Pediatric Patients: Dosage based on body weight (see Table 2).

Renal Impairment (2.3):

- Do not use for prophylaxis of malaria in patients with severe renal impairment.
- Use with caution for treatment of malaria in patients with severe renal impairment.

3 DOSAGE FORMS AND STRENGTHS

- Tablets (adult strength): 250 mg atovaquone and 100 mg proguanil hydrochloride. (3)
- Pediatric tablets: 62.5 mg atovaquone and 25 mg proguanil hydrochloride. (3)

4 CONTRAINDICATIONS

- Known serious hypersensitivity reactions to atovaquone or proguanil hydrochloride or any component of the formulation. (4)
- Prophylaxis of P. falciparum malaria in patients with severe renal impairment (creatinine clearance <30 mL/min). (4)

5 WARNINGS AND PRECAUTIONS

- Atovaquone absorption may be reduced in patients with diarrhea or vomiting. If used in patients who are vomiting, parasitemia should be closely monitored and the use of an antiemetic considered. In patients with severe or persistent diarrhea or vomiting, alternative antimalarial therapy may be required. (5.1)
- In mixed P. falciparum and Plasmodium vivax infection, P. vivax relapse occurred commonly when patients were treated with MALARONE alone. (5.2)
- In the event of recrudescent P. falciparum infections after treatment or prophylaxis failure, patients should be treated with a different blood schizonticide. (5.2)
- Elevated liver laboratory tests and cases of hepatitis and hepatic failure requiring liver transplantation have been reported with prophylactic use. (5.3)
- MALARONE has not been evaluated for the treatment of cerebral malaria or other severe manifestations of complicated malaria. Patients with severe malaria are not candidates for oral therapy. (5.4)

6 ADVERSE REACTIONS

- Prophylaxis: Common adverse reactions (≥4%) in adults were diarrhea, dreams, oral ulcers, and headache; these events occurred in a similar or lower proportion of subjects receiving MALARONE than an active comparator. Common adverse reactions (≥5%) in pediatric patients included abdominal pain, headache, cough, and vomiting. (6.1)
- Treatment: Common adverse reactions (≥5%) in adolescents and adults were abdominal pain, nausea, vomiting, headache, diarrhea, asthenia, anorexia, and dizziness. Common adverse reactions (≥6%) in pediatric patients included vomiting, pruritus, and diarrhea. (6.1)

To report SUSPECTED ADVERSE REACTIONS, contact GlaxoSmithKline at 1-888-825-5249 or FDA at 1-800-FDA-1088 or www.fda.gov/medwatch.

7 DRUG INTERACTIONS

- Administration with rifampin or rifabutin is known to reduce atovaquone concentrations; concomitant use with MALARONE is not recommended. (7.1)
- Proguanil may potentiate anticoagulant effect of warfarin and other coumarin-based anticoagulants. Caution advised when initiating or withdrawing MALARONE in patients on anticoagulants; coagulation tests should be closely monitored. (7.2)
- Tetracycline may reduce atovaquone concentrations; parasitemia should be closely monitored. (7.3)

8 USE IN SPECIFIC POPULATIONS

Renal impairment: contraindicated for prophylaxis of P. falciparum malaria in patients with severe renal impairment. (8.6)

FULL PRESCRIBING INFORMATION

1 INDICATIONS AND USAGE

1.1 Prevention of Malaria

MALARONE is indicated for the prophylaxis of Plasmodium falciparum malaria, including in areas where chloroquine resistance has been reported.

1.2 Treatment of Malaria

MALARONE is indicated for the treatment of acute, uncomplicated P. falciparum malaria. MALARONE has been shown to be effective in regions where the drugs chloroquine, halofantrine, mefloquine, and amodiaquine may have unacceptable failure rates, presumably due to drug resistance.

2 DOSAGE AND ADMINISTRATION

The daily dose should be taken at the same time each day with food or a milky drink. In the event of vomiting within 1 hour after dosing, a repeat dose should be taken.

MALARONE may be crushed and mixed with condensed milk just prior to administration to patients who may have difficulty swallowing tablets.

2.1 Prevention of Malaria

Start prophylactic treatment with MALARONE 1 or 2 days before entering a malaria‑endemic area and continue daily during the stay and for 7 days after return.

Adults

One MALARONE tablet (adult strength = 250 mg atovaquone/100 mg proguanil hydrochloride) per day.

Pediatric Patients

The dosage for prevention of malaria in pediatric patients is based upon body weight (Table 1).

Table 1. Dosage for Prevention of Malaria in Pediatric Patients
Weight; (kg) | Atovaquone/; Proguanil HCl; Total Daily Dose | Dosage Regimen
11-20 | 62.5 mg/25 mg | 1 MALARONE pediatric tablet daily
21-30 | 125 mg/50 mg | 2 MALARONE pediatric tablets as a single daily dose
31-40 | 187.5 mg/75 mg | 3 MALARONE pediatric tablets as a single daily dose
>40 | 250 mg/100 mg | 1 MALARONE tablet (adult strength) as a single daily dose

2.2 Treatment of Acute Malaria

Adults

Four MALARONE tablets (adult strength; total daily dose 1 g atovaquone/400 mg proguanil hydrochloride) as a single daily dose for 3 consecutive days.

Pediatric Patients

The dosage for treatment of acute malaria in pediatric patients is based upon body weight (Table 2).

Table 2. Dosage for Treatment of Acute Malaria in Pediatric Patients
Weight; (kg) | Atovaquone/; Proguanil HCl; Total Daily Dose | Dosage Regimen
5-8 | 125 mg/50 mg | 2 MALARONE pediatric tablets daily for 3 consecutive days
9-10 | 187.5 mg/75 mg | 3 MALARONE pediatric tablets daily for 3 consecutive days
11-20 | 250 mg/100 mg | 1 MALARONE tablet (adult strength) daily for 3 consecutive days
21-30 | 500 mg/200 mg | 2 MALARONE tablets (adult strength) as a single daily dose for 3 consecutive days
31-40 | 750 mg/300 mg | 3 MALARONE tablets (adult strength) as a single daily dose for 3 consecutive days
>40 | 1 g/400 mg | 4 MALARONE tablets (adult strength) as a single daily dose for 3 consecutive days

2.3 Renal Impairment

Do not use MALARONE for malaria prophylaxis in patients with severe renal impairment (creatinine clearance <30 mL/min) [see Contraindications (4.2)]. Use with caution for the treatment of malaria in patients with severe renal impairment, only if the benefits of the 3-day treatment regimen outweigh the potential risks associated with increased drug exposure. No dosage adjustments are needed in patients with mild (creatinine clearance 50 to 80 mL/min) or moderate (creatinine clearance 30 to 50 mL/min) renal impairment. [See Clinical Pharmacology (12.3).]

3 DOSAGE FORMS AND STRENGTHS

Each MALARONE tablet (adult strength) contains 250 mg atovaquone and 100 mg proguanil hydrochloride. MALARONE tablets are pink, film‑coated, round, biconvex tablets engraved with “GX CM3” on one side.

Each MALARONE pediatric tablet contains 62.5 mg atovaquone and 25 mg proguanil hydrochloride. MALARONE pediatric tablets are pink, film‑coated, round, biconvex tablets engraved with “GX CG7” on one side.

4 CONTRAINDICATIONS

- MALARONE is contraindicated in individuals with known hypersensitivity reactions (e.g., anaphylaxis, erythema multiforme or Stevens-Johnson syndrome, angioedema, vasculitis) to atovaquone or proguanil hydrochloride or any component of the formulation.
- MALARONE is contraindicated for prophylaxis of P. falciparum malaria in patients with severe renal impairment (creatinine clearance <30 mL/min) because of pancytopenia in patients with severe renal impairment treated with proguanil [see Use in Specific Populations (8.6), Clinical Pharmacology (12.3)].

5 WARNINGS AND PRECAUTIONS

5.1 Vomiting and Diarrhea

Absorption of atovaquone may be reduced in patients with diarrhea or vomiting. If MALARONE is used in patients who are vomiting, parasitemia should be closely monitored and the use of an antiemetic considered. [See Dosage and Administration (2).] Vomiting occurred in up to 19% of pediatric patients given treatment doses of MALARONE. In the controlled clinical trials, 15.3% of adults received an antiemetic when they received atovaquone/proguanil and 98.3% of these patients were successfully treated. In patients with severe or persistent diarrhea or vomiting, alternative antimalarial therapy may be required.

5.2 Relapse of Infection

In mixed P. falciparum and Plasmodium vivax infections, P. vivax parasite relapse occurred commonly when patients were treated with MALARONE alone.

In the event of recrudescent P. falciparum infections after treatment with MALARONE or failure of chemoprophylaxis with MALARONE, patients should be treated with a different blood schizonticide.

5.3 Hepatotoxicity

Elevated liver laboratory tests and cases of hepatitis and hepatic failure requiring liver transplantation have been reported with prophylactic use of MALARONE.

5.4 Severe or Complicated Malaria

MALARONE has not been evaluated for the treatment of cerebral malaria or other severe manifestations of complicated malaria, including hyperparasitemia, pulmonary edema, or renal failure. Patients with severe malaria are not candidates for oral therapy.

6 ADVERSE REACTIONS

6.1 Clinical Trials Experience

Because clinical trials are conducted under widely varying conditions, adverse reaction rates observed in the clinical trials of a drug cannot be directly compared with rates in the clinical trials of another drug and may not reflect the rates observed in practice.

Because MALARONE contains atovaquone and proguanil hydrochloride, the type and severity of adverse reactions associated with each of the compounds may be expected. The lower prophylactic doses of MALARONE were better tolerated than the higher treatment doses.

Prophylaxis of P. falciparum Malaria

In 3 clinical trials (2 of which were placebo‑controlled) 381 adults (mean age: 31 years) received MALARONE for the prophylaxis of malaria; the majority of adults were black (90%) and 79% were male. In a clinical trial for the prophylaxis of malaria, 125 pediatric patients (mean age: 9 years) received MALARONE; all subjects were black and 52% were male. Adverse experiences reported in adults and pediatric patients considered attributable to therapy occurred in similar proportions of subjects receiving MALARONE or placebo in all studies. Prophylaxis with MALARONE was discontinued prematurely due to a treatment‑related adverse experience in 3 of 381 (0.8%) adults and 0 of 125 pediatric patients.

In a placebo‑controlled study of malaria prophylaxis with MALARONE involving 330 pediatric patients (aged 4 to 14 years) in Gabon, a malaria‑endemic area, the safety profile of MALARONE was consistent with that observed in the earlier prophylactic studies in adults and pediatric patients. The most common treatment‑emergent adverse events with MALARONE were abdominal pain (13%), headache (13%), and cough (10%). Abdominal pain (13% vs. 8%) and vomiting (5% vs. 3%) were reported more often with MALARONE than with placebo. No patient withdrew from the study due to an adverse experience with MALARONE. No routine laboratory data were obtained during this study.

Non‑immune travelers visiting a malaria‑endemic area received MALARONE (n = 1,004) for prophylaxis of malaria in 2 active-controlled clinical trials. In one study (n = 493), the mean age of subjects was 33 years and 53% were male; 90% of subjects were white, 6% of subjects were black, and the remaining were of other racial/ethnic groups. In the other study (n = 511), the mean age of subjects was 36 years and 51% were female; the majority of subjects (97%) were white. Adverse experiences occurred in a similar or lower proportion of subjects receiving MALARONE than an active comparator (Table 3). Fewer neuropsychiatric adverse experiences occurred in subjects who received MALARONE than mefloquine. Fewer gastrointestinal adverse experiences occurred in subjects receiving MALARONE than chloroquine/proguanil. Compared with active comparator drugs, subjects receiving MALARONE had fewer adverse experiences overall that were attributed to prophylactic therapy (Table 3). Prophylaxis with MALARONE was discontinued prematurely due to a treatment‑related adverse experience in 7 of 1,004 travelers.

Table 3. Adverse Experiences in ActiveControlled Clinical Trials of MALARONE for Prophylaxis of P. falciparum Malaria
Adverse; Experience | Percent of Subjects with Adverse Experiencesa; (Percent of Subjects with Adverse Experiences Attributable to Therapy)
Adverse; Experience | Study 1 |  |  |  | Study 2
Adverse; Experience | MALARONE; n = 493; (28 days)b |  | Mefloquine; n = 483; (53 days)b |  | MALARONE; n = 511; (26 days)b |  | Chloroquine plus Proguanil; n = 511; (49 days)b
Diarrhea | 38 | (8) | 36 | (7) | 34 | (5) | 39 | (7)
Nausea | 14 | (3) | 20 | (8) | 11 | (2) | 18 | (7)
Abdominal pain | 17 | (5) | 16 | (5) | 14 | (3) | 22 | (6)
Headache | 12 | (4) | 17 | (7) | 12 | (4) | 14 | (4)
Dreams | 7 | (7) | 16 | (14) | 6 | (4) | 7 | (3)
Insomnia | 5 | (3) | 16 | (13) | 4 | (2) | 5 | (2)
Fever | 9 | (<1) | 11 | (1) | 8 | (<1) | 8 | (<1)
Dizziness | 5 | (2) | 14 | (9) | 7 | (3) | 8 | (4)
Vomiting | 8 | (1) | 10 | (2) | 8 | (0) | 14 | (2)
Oral ulcers | 9 | (6) | 6 | (4) | 5 | (4) | 7 | (5)
Pruritus | 4 | (2) | 5 | (2) | 3 | (1) | 2 | (<1)
Visual difficulties | 2 | (2) | 5 | (3) | 3 | (2) | 3 | (2)
Depression | <1 | (<1) | 5 | (4) | <1 | (<1) | 1 | (<1)
Anxiety | 1 | (<1) | 5 | (4) | <1 | (<1) | 1 | (<1)
Any adverse experience | 64 | (30) | 69 | (42) | 58 | (22) | 66 | (28)
Any neuropsychiatric event | 20 | (14) | 37 | (29) | 16 | (10) | 20 | (10)
Any GI event | 49 | (16) | 50 | (19) | 43 | (12) | 54 | (20)
a Adverse experiences that started while receiving active study drug.
b Mean duration of dosing based on recommended dosing regimens.

In a third active‑controlled study, MALARONE (n = 110) was compared with chloroquine/proguanil (n = 111) for the prophylaxis of malaria in 221 non-immune pediatric patients (aged 2 to 17 years). The mean duration of exposure was 23 days for MALARONE, 46 days for chloroquine, and 43 days for proguanil, reflecting the different recommended dosage regimens for these products. Fewer patients treated with MALARONE reported abdominal pain (2% vs. 7%) or nausea (<1% vs. 7%) than children who received chloroquine/proguanil. Oral ulceration (2% vs. 2%), vivid dreams (2% vs. <1%), and blurred vision (0% vs. 2%) occurred in similar proportions of patients receiving either MALARONE or chloroquine/proguanil, respectively. Two patients discontinued prophylaxis with chloroquine/proguanil due to adverse events, while none of those receiving MALARONE discontinued due to adverse events.

Treatment of Acute, Uncomplicated P. falciparum Malaria

In 7 controlled trials, 436 adolescents and adults received MALARONE for treatment of acute, uncomplicated P. falciparum malaria. The range of mean ages of subjects was 26 to 29 years; 79% of subjects were male. In these studies, 48% of subjects were classified as other racial/ethnic groups, primarily Asian; 42% of subjects were black and the remaining subjects were white. Attributable adverse experiences that occurred in ≥5% of patients were abdominal pain (17%), nausea (12%), vomiting (12%), headache (10%), diarrhea (8%), asthenia (8%), anorexia (5%), and dizziness (5%). Treatment was discontinued prematurely due to an adverse experience in 4 of 436 (0.9%) adolescents and adults treated with MALARONE.

In 2 controlled trials, 116 pediatric patients (weighing 11 to 40 kg) (mean age: 7 years) received MALARONE for the treatment of malaria. The majority of subjects were black (72%); 28% were of other racial/ethnic groups, primarily Asian. Attributable adverse experiences that occurred in ≥5% of patients were vomiting (10%) and pruritus (6%). Vomiting occurred in 43 of 319 (13%) pediatric patients who did not have symptomatic malaria but were given treatment doses of MALARONE for 3 days in a clinical trial. The design of this clinical trial required that any patient who vomited be withdrawn from the trial. Among pediatric patients with symptomatic malaria treated with MALARONE, treatment was discontinued prematurely due to an adverse experience in 1 of 116 (0.9%).

In a study of 100 pediatric patients (5 to <11 kg body weight) who received MALARONE for the treatment of uncomplicated P. falciparum malaria, only diarrhea (6%) occurred in ≥5% of patients as an adverse experience attributable to MALARONE. In 3 patients (3%), treatment was discontinued prematurely due to an adverse experience.

Abnormalities in laboratory tests reported in clinical trials were limited to elevations of transaminases in patients with malaria being treated with MALARONE. The frequency of these abnormalities varied substantially across trials of treatment and were not observed in the randomized portions of the prophylaxis trials.

One active-controlled trial evaluated the treatment of malaria in Thai adults (n = 182); the mean age of subjects was 26 years (range: 15 to 63 years); 80% of subjects were male. Early elevations of ALT and AST occurred more frequently in patients treated with MALARONE (n = 91) compared with patients treated with an active control, mefloquine (n = 91). On Day 7, rates of elevated ALT and AST with MALARONE and mefloquine (for patients who had normal baseline levels of these clinical laboratory parameters) were ALT 26.7% vs. 15.6%; AST 16.9% vs. 8.6%, respectively. By Day 14 of this 28‑day study, the frequency of transaminase elevations equalized across the 2 groups.

6.2 Postmarketing Experience

In addition to adverse events reported from clinical trials, the following events have been identified during postmarketing use of MALARONE. Because they are reported voluntarily from a population of unknown size, estimates of frequency cannot be made. These events have been chosen for inclusion due to a combination of their seriousness, frequency of reporting, or potential causal connection to MALARONE.

Blood and Lymphatic System Disorders

Neutropenia and anemia. Pancytopenia in patients with severe renal impairment treated with proguanil [see Contraindications (4.2)].

Immune System Disorders

Allergic reactions including anaphylaxis, angioedema, urticaria, and vasculitis.

Nervous System Disorders

Seizures and psychotic events (such as hallucinations); however, a causal relationship has not been established.

Gastrointestinal Disorders

Stomatitis.

Hepatobiliary Disorders

Elevated liver laboratory tests, hepatitis, cholestasis; hepatic failure requiring transplant has been reported.

Skin and Subcutaneous Tissue Disorders

Photosensitivity, rash, erythema multiforme, and Stevens-Johnson syndrome.

7 DRUG INTERACTIONS

7.1 Rifampin/Rifabutin

Concomitant administration of rifampin or rifabutin is known to reduce atovaquone concentrations [see Clinical Pharmacology (12.3)]. The concomitant administration of MALARONE and rifampin or rifabutin is not recommended.

7.2 Anticoagulants

Proguanil may potentiate the anticoagulant effect of warfarin and other coumarin-based anticoagulants. The mechanism of this potential drug interaction has not been established. Caution is advised when initiating or withdrawing malaria prophylaxis or treatment with MALARONE in patients on continuous treatment with coumarin-based anticoagulants. When these products are administered concomitantly, coagulation tests should be closely monitored.

7.3 Tetracycline

Concomitant treatment with tetracycline has been associated with a reduction in plasma concentrations of atovaquone [see Clinical Pharmacology (12.3)]. Parasitemia should be closely monitored in patients receiving tetracycline.

7.4 Metoclopramide

While antiemetics may be indicated for patients receiving MALARONE, metoclopramide may reduce the bioavailability of atovaquone and should be used only if other antiemetics are not available [see Clinical Pharmacology (12.3)].

7.5 Indinavir

Concomitant administration of atovaquone and indinavir did not result in any change in the steady‑state AUC and Cmax of indinavir but resulted in a decrease in the Ctrough of indinavir [see Clinical Pharmacology (12.3)]. Caution should be exercised when prescribing atovaquone with indinavir due to the decrease in trough concentrations of indinavir.

8 USE IN SPECIFIC POPULATIONS

8.1 Pregnancy

Risk Summary

Available data from published literature and postmarketing experience with use of MALARONE in pregnant women are insufficient to identify a drug-associated risk for major birth defects, miscarriage, or adverse maternal or fetal outcomes. The proguanil component of MALARONE acts to inhibit parasitic dihydrofolate reductase; however, pregnant women and females of reproductive potential should continue folate supplementation to prevent neural tube defects [see Clinical Pharmacology (12.4)]. Pregnant women with malaria are at increased risk for adverse pregnancy outcomes (see Clinical Considerations).

Atovaquone administered by oral gavage to pregnant rats and rabbits during the period of organogenesis was not associated with fetal malformations at plasma exposures approximately 7 times and equal to, respectively, the estimated human exposure for the treatment of malaria based on AUC. Proguanil administered to pregnant rats and rabbits during the period of organogenesis was not associated with embryo-fetal toxicity at maternally toxic plasma exposures approximately 0.07 and 0.8 times, respectively, the estimated human exposure for treatment of malaria based on AUC (see Data).

The combination of atovaquone and proguanil hydrochloride given orally by gavage during the period of organogenesis was not associated with embryo-fetal developmental effects in pregnant rats or rabbits at atovaquone:proguanil hydrochloride doses of 50:20 mg/kg/day and 100:40 mg/kg/day, respectively (1.7 and 0.1 times and 0.3 and 0.5 times, respectively, the estimated human exposure for treatment of malaria). In a pre- and post-natal study with atovaquone and another pre-and post-natal study with proguanil, neither compound impaired the growth, development, or reproductive ability of first-generation offspring at maternal AUC exposures of approximately 7.3 and 0.04 times, respectively, the estimated human AUC exposure for treatment of malaria (see Data).

The estimated background risk of major birth defects and miscarriage for the indicated population is unknown. All pregnancies have a background risk of birth defect, loss, or other adverse outcomes. In the U.S. general population, the background risk of major birth defects and miscarriage in clinically recognized pregnancies is 2% to 4% and 15% to 20%, respectively.

Clinical Considerations

Disease-Associated Maternal and/or Embryo/Fetal Risk: Malaria during pregnancy increases the risk for adverse pregnancy outcomes, including maternal anemia, prematurity, spontaneous abortion, and stillbirth.

Data

Animal Data: Atovaquone: Atovaquone administered in oral doses of 250, 500, and 1,000 mg/kg/day during organogenesis (Gestation Day [GD] 6 to GD15) in pregnant rats did not cause maternal or embryo-fetal toxicity at doses up to 1,000 mg/kg/day corresponding to maternal plasma exposures up to 7.3 times the estimated human exposure for the treatment of malaria based on AUC. In pregnant rabbits, atovaquone administered in oral doses of 300, 600, and 1,200 mg/kg/day by gavage during organogenesis (GD6 to GD18) was associated with decreased fetal body length at a maternally toxic dose of 1,200 mg/kg/day corresponding to plasma exposures that were approximately 1.3 times the estimated human exposure during treatment of malaria based on AUC. In a pre- and post-natal study in rats, atovaquone administered in oral doses of 250, 500, and 1,000 mg/kg/day from GD15 until Lactation Day (LD) 20 did not impair the growth or developmental effects in first-generation offspring at doses up to 1,000 mg/kg/day corresponding to AUC exposures of approximately 7.3 times the estimated human exposure during treatment of malaria. Atovaquone crossed the placenta and was present in fetal rat and rabbit tissue.

Proguanil: Proguanil administered orally to pregnant rats during organogenesis (GD6 to GD17) was not associated with fetal malformations, but increased ureter variations at a maternally toxic dose of 20 mg/kg/day corresponding to a plasma concentration approximately equal to 0.07 times the estimated human exposure for the treatment of malaria based on AUC. Proguanil given orally by gavage at a maternally toxic dose of 40 mg/kg/day to pregnant rabbits during organogenesis (GD6 to GD20) did not produce adverse embryo-fetal effects at a plasma concentration up to 0.8 times the estimated human exposure for the treatment of malaria based on AUC. In a pre- and post-natal study in female rats, proguanil hydrochloride administered in oral doses of 4, 8, or 16 mg/kg/day from GD6 until LD20 did not impair the growth, development, or reproductive ability of first-generation offspring or the survivability of second generation offspring at doses up to 16 mg/kg/day (0.04 times the average human exposure based on AUC). Pre- and post-natal studies of proguanil in animals at exposures similar to or greater than those observed in humans have not been conducted.

Atovaquone and Proguanil: The combination of atovaquone and proguanil hydrochloride administered orally to pregnant rats in atovaquone:proguanil hydrochloride doses of 12.5:5, 25:10, and 50:20 mg/kg/day during organogenesis (GD6 to GD17) did not produce maternal toxicity or adverse embryo-fetal developmental effects with doses up to 50:20 mg/kg/day corresponding to plasma concentrations up to 1.7 and 0.1 times, respectively, the estimated human exposure during treatment of malaria based on AUC. In pregnant rabbits, the combination of atovaquone and proguanil hydrochloride administered orally in atovaquone:proguanil hydrochloride doses of 25:10, 50:20, or 100:40 mg/kg/day during organogenesis (GD6 to GD20) did not produce adverse embryo-fetal developmental effects at a maternally toxic dose of 100:40 mg/kg/day corresponding to plasma concentrations of approximately 0.3 and 0.5 times, respectively, the estimated human exposure during treatment of malaria based on AUC.

8.2 Lactation

Risk Summary

There are no data on the presence of atovaquone in human milk; however, proguanil is present in human milk. Atovaquone is present in rat milk (see Data). When a drug is present in animal milk, it is likely the drug will be present in human milk. There are no data on the effects of atovaquone and proguanil on the breastfed child or the effects on milk production. The developmental and health benefits of breastfeeding should be considered along with the mother’s clinical need for MALARONE and any potential adverse effect on the breastfed child from MALARONE or from the underlying maternal condition.

Data

In a rat study with doses of 10 and 250 mg/kg, given orally by gavage on postpartum Day 11, atovaquone concentrations in the milk were 30% of the concurrent atovaquone concentrations in the maternal plasma at both doses. The concentration of drug in animal milk does not necessarily predict the concentration of drug in human milk.

8.4 Pediatric Use

Prophylaxis of Malaria

Safety and effectiveness have not been established in pediatric patients who weigh less than 11 kg. The efficacy and safety of MALARONE have been established for the prophylaxis of malaria in controlled trials involving pediatric patients weighing 11 kg or more [see Clinical Studies (14.1)].

Treatment of Malaria

Safety and effectiveness have not been established in pediatric patients who weigh less than 5 kg. The efficacy and safety of MALARONE for the treatment of malaria have been established in controlled trials involving pediatric patients weighing 5 kg or more [see Clinical Studies (14.2)].

8.5 Geriatric Use

Clinical trials of MALARONE did not include sufficient numbers of subjects aged 65 years and older to determine whether they respond differently from younger subjects. In general, dose selection for an elderly patient should be cautious, reflecting the greater frequency of decreased hepatic, renal, or cardiac function, the higher systemic exposure to cycloguanil, and the greater frequency of concomitant disease or other drug therapy. [See Clinical Pharmacology (12.3).]

8.6 Renal Impairment

Do not use MALARONE for malaria prophylaxis in patients with severe renal impairment (creatinine clearance <30 mL/min). Use with caution for the treatment of malaria in patients with severe renal impairment only if the benefits of the 3-day treatment regimen outweigh the potential risks associated with increased drug exposure. No dosage adjustments are needed in patients with mild (creatinine clearance 50 to 80 mL/min) or moderate (creatinine clearance 30 to 50 mL/min) renal impairment. [See Clinical Pharmacology (12.3).]

8.7 Hepatic Impairment

No dosage adjustments are needed in patients with mild or moderate hepatic impairment [see Clinical Pharmacology (12.3)]. No trials have been conducted in patients with severe hepatic impairment.

10 OVERDOSAGE

There is no information on overdoses of MALARONE substantially higher than the doses recommended for treatment.

There is no known antidote for atovaquone, and it is currently unknown if atovaquone is dialyzable. Overdoses up to 31,500 mg of atovaquone have been reported. In one such patient who also took an unspecified dose of dapsone, methemoglobinemia occurred. Rash has also been reported after overdose.

Overdoses of proguanil hydrochloride as large as 1,500 mg have been followed by complete recovery, and doses as high as 700 mg twice daily have been taken for over 2 weeks without serious toxicity. Adverse experiences occasionally associated with proguanil hydrochloride doses of 100 to 200 mg/day, such as epigastric discomfort and vomiting, would be likely to occur with overdose. There are also reports of reversible hair loss and scaling of the skin on the palms and/or soles, reversible aphthous ulceration, and hematologic side effects.

11 DESCRIPTION

MALARONE (atovaquone and proguanil hydrochloride) tablets (adult strength) and MALARONE (atovaquone and proguanil hydrochloride) pediatric tablets, for oral administration, contain a fixed‑dose combination of the antimalarial agents atovaquone and proguanil hydrochloride.

The chemical name of atovaquone is trans-2-[4-(4-chlorophenyl)cyclohexyl]-3-hydroxy-1,4-naphthalenedione. Atovaquone is a yellow crystalline solid that is practically insoluble in water. It has a molecular weight of 366.84 and the molecular formula C22H19ClO3. The compound has the following structural formula:

The chemical name of proguanil hydrochloride is 1-(4-chlorophenyl)-5-isopropyl-biguanide hydrochloride. Proguanil hydrochloride is a white crystalline solid that is sparingly soluble in water. It has a molecular weight of 290.22 and the molecular formula C11H16ClN5•HCl. The compound has the following structural formula:

Each MALARONE tablet (adult strength) contains 250 mg of atovaquone and 100 mg of proguanil hydrochloride and each MALARONE pediatric tablet contains 62.5 mg of atovaquone and 25 mg of proguanil hydrochloride. The inactive ingredients in both tablets are low‑substituted hydroxypropyl cellulose, magnesium stearate, microcrystalline cellulose, poloxamer 188, povidone K30, and sodium starch glycolate. The tablet coating contains hypromellose, polyethylene glycol 400, polyethylene glycol 8000, red iron oxide, and titanium dioxide.

12 CLINICAL PHARMACOLOGY

12.1 Mechanism of Action

MALARONE, a fixed-dose combination of atovaquone and proguanil hydrochloride, is an antimalarial agent [see Microbiology (12.4)].

12.2 Pharmacodynamics

Cardiac Effects

The effect of MALARONE on the QT interval is unknown in humans.

12.3 Pharmacokinetics

Absorption

Atovaquone is a highly lipophilic compound with low aqueous solubility. The bioavailability of atovaquone shows considerable inter‑individual variability.

Effect of Food: MALARONE should be taken with food or a milky drink. Dietary fat taken with atovaquone increases the rate and extent of absorption, increasing AUC 2 to 3 times and Cmax 5 times over fasting. The absolute bioavailability of the tablet formulation of atovaquone when taken with food is 23%.

Distribution

Atovaquone is highly protein bound (>99%) over the concentration range of 1 to 90 mcg/mL. A population pharmacokinetic analysis demonstrated that the apparent volume of distribution of atovaquone (V/F) in adult and pediatric patients after oral administration is approximately 8.8 L/kg.

Proguanil is 75% protein bound. A population pharmacokinetic analysis demonstrated that the apparent V/F of proguanil in adult and pediatric patients older than 15 years with body weights from 31 to 110 kg ranged from 1,617 to 2,502 L. In pediatric patients 15 years and younger with body weights from 11 to 56 kg, the V/F of proguanil ranged from 462 to 966 L.

In human plasma, the binding of atovaquone and proguanil was unaffected by the presence of the other.

Elimination

The elimination half‑life of atovaquone is about 2 to 3 days in adult patients. The elimination half‑life of proguanil is 12 to 21 hours in both adult patients and pediatric patients but may be longer in individuals who are slow metabolizers.

The main routes of elimination are hepatic biotransformation and renal excretion.

Metabolism: In a study where ^14C‑labeled atovaquone was administered to healthy volunteers, greater than 94% of the dose was recovered as unchanged atovaquone in the feces over 21 days. There was little or no excretion of atovaquone in the urine (less than 0.6%). There is indirect evidence that atovaquone may undergo limited metabolism; however, a specific metabolite has not been identified. Between 40% to 60% of proguanil is excreted by the kidneys. Proguanil is metabolized to cycloguanil (primarily via cytochrome P450 2C19 [CYP2C19]) and 4-chlorophenylbiguanide.

Excretion: A population pharmacokinetic analysis in adult and pediatric patients showed that the apparent clearance (CL/F) of both atovaquone and proguanil is related to body weight. The values CL/F for both atovaquone and proguanil in subjects with body weight ≥11 kg are shown in Table 4.

Table 4. Apparent Clearance for Atovaquone and Proguanil in Patients as a Function of Body Weight
Body Weight | Atovaquone |  | Proguanil
Body Weight | n | CL/F (L/h); Mean ± SDa (range) | n | CL/F (L/h); Mean ± SDa (range)
11-20 kg | 159 | 1.34 ± 0.63; (0.52-4.26) | 146 | 29.5 ± 6.5; (10.3-48.3)
21-30 kg | 117 | 1.87 ± 0.81; (0.52-5.38) | 113 | 40.0 ± 7.5; (15.9-62.7)
31-40 kg | 95 | 2.76 ± 2.07; (0.97-12.5) | 91 | 49.5 ± 8.30; (25.8-71.5)
>40 kg | 368 | 6.61 ± 3.92; (1.32-20.3) | 282 | 67.9 ± 19.9; (14.0-145)
a SD = Standard deviation.

The pharmacokinetics of atovaquone and proguanil in patients with body weight less than 11 kg have not been adequately characterized.

Specific Populations

Pediatric Patients: The pharmacokinetics of proguanil and cycloguanil are similar in adult patients and pediatric patients. However, the elimination half‑life of atovaquone is shorter in pediatric patients (1 to 2 days) than in adult patients (2 to 3 days). In clinical trials, plasma trough concentrations of atovaquone and proguanil in pediatric patients weighing 5 to 40 kg were within the range observed in adults after dosing by body weight.

Geriatric Patients: In a single‑dose study, the pharmacokinetics of atovaquone, proguanil, and cycloguanil were compared in 13 elderly subjects (aged 65 to 79 years) with those of 13 younger subjects (aged 30 to 45 years). In the elderly subjects, the extent of systemic exposure (AUC) of cycloguanil was increased (point estimate: 2.36, 90% CI: 1.70, 3.28). Tmax was longer in elderly subjects (median: 8 hours) compared with younger subjects (median: 4 hours) and average elimination half‑life was longer in elderly subjects (mean: 14.9 hours) compared with younger subjects (mean: 8.3 hours).

Patients with Renal Impairment: In patients with mild renal impairment (creatinine clearance 50 to 80 mL/min), oral clearance and/or AUC data for atovaquone, proguanil, and cycloguanil are within the range of values observed in patients with normal renal function (creatinine clearance >80 mL/min). In patients with moderate renal impairment (creatinine clearance 30 to 50 mL/min), mean oral clearance for proguanil was reduced by approximately 35% compared with patients with normal renal function (creatinine clearance >80 mL/min) and the oral clearance of atovaquone was comparable between patients with normal renal function and mild renal impairment. No data exist on the use of MALARONE for long-term prophylaxis (over 2 months) in individuals with moderate renal failure. In patients with severe renal impairment (creatinine clearance <30 mL/min), atovaquone Cmax and AUC are reduced but the elimination half‑lives for proguanil and cycloguanil are prolonged, with corresponding increases in AUC, resulting in the potential of drug accumulation and toxicity with repeated dosing [see Contraindications (4.2)].

Patients with Hepatic Impairment: In a single‑dose study, the pharmacokinetics of atovaquone, proguanil, and cycloguanil were compared in 13 subjects with hepatic impairment (9 mild, 4 moderate, as indicated by the Child‑Pugh method) with those of 13 subjects with normal hepatic function. In subjects with mild or moderate hepatic impairment as compared with healthy subjects, there were no marked differences (<50%) in the rate or extent of systemic exposure of atovaquone. However, in subjects with moderate hepatic impairment, the elimination half‑life of atovaquone was increased (point estimate: 1.28, 90% CI: 1.00 to 1.63). Proguanil AUC, Cmax, and its elimination half‑life increased in subjects with mild hepatic impairment when compared with healthy subjects (Table 5). Also, the proguanil AUC and its elimination half‑life increased in subjects with moderate hepatic impairment when compared with healthy subjects. Consistent with the increase in proguanil AUC, there were marked decreases in the systemic exposure of cycloguanil (Cmax and AUC) and an increase in its elimination half‑life in subjects with mild hepatic impairment when compared with healthy volunteers (Table 5). There were few measurable cycloguanil concentrations in subjects with moderate hepatic impairment. The pharmacokinetics of atovaquone, proguanil, and cycloguanil after administration of MALARONE have not been studied in patients with severe hepatic impairment.

Table 5. Point Estimates (90% CI) for Proguanil and Cycloguanil Parameters in Subjects with Mild and Moderate Hepatic Impairment Compared with Healthy Volunteers
Parameter | Comparison | Proguanil | Cycloguanil
AUC(0-inf)a | mild:healthy | 1.96 (1.51, 2.54) | 0.32 (0.22, 0.45)
Cmaxa | mild:healthy | 1.41 (1.16, 1.71) | 0.35 (0.24, 0.50)
t1/2b | mild:healthy | 1.21 (0.92, 1.60) | 0.86 (0.49, 1.48)
AUC(0-inf)a | moderate:healthy | 1.64 (1.14, 2.34) | ND
Cmaxa | moderate:healthy | 0.97 (0.69, 1.36) | ND
t1/2b | moderate:healthy | 1.46 (1.05, 2.05) | ND
ND = Not determined due to lack of quantifiable data.
a Ratio of geometric means.
b Mean difference.

Drug Interaction Studies

There are no pharmacokinetic interactions between atovaquone and proguanil at the recommended dose.

Atovaquone is highly protein bound (>99%) but does not displace other highly protein‑bound drugs in vitro.

Proguanil is metabolized primarily by CYP2C19. Potential pharmacokinetic interactions between proguanil or cycloguanil and other drugs that are CYP2C19 substrates or inhibitors are unknown.

Rifampin/Rifabutin: Concomitant administration of rifampin or rifabutin is known to reduce atovaquone concentrations by approximately 50% and 34%, respectively. The mechanisms of these interactions are unknown.

Tetracycline: Concomitant treatment with tetracycline has been associated with approximately a 40% reduction in plasma concentrations of atovaquone.

Metoclopramide: Concomitant treatment with metoclopramide has been associated with decreased bioavailability of atovaquone.

Indinavir: Concomitant administration of atovaquone (750 mg twice daily with food for 14 days) and indinavir (800 mg three times daily without food for 14 days) did not result in any change in the steady‑state AUC and Cmax of indinavir but resulted in a decrease in the Ctrough of indinavir (23% decrease [90% CI: 8%, 35%]).

12.4 Microbiology

Mechanism of Action

The constituents of MALARONE, atovaquone and proguanil hydrochloride, interfere with 2 different pathways involved in the biosynthesis of pyrimidines required for nucleic acid replication. Atovaquone is a selective inhibitor of parasite mitochondrial electron transport. Proguanil hydrochloride primarily exerts its effect by means of the metabolite cycloguanil, a dihydrofolate reductase inhibitor. Inhibition of dihydrofolate reductase in the Plasmodium parasite disrupts deoxythymidylate synthesis.

Antimicrobial Activity

Atovaquone and cycloguanil (an active metabolite of proguanil) are active against the erythrocytic and exoerythrocytic stages of P. falciparum. Enhanced efficacy of the combination compared with either atovaquone or proguanil hydrochloride alone was demonstrated in clinical trials in both immune and non-immune patients [see Clinical Studies (14.1, 14.2)].

Resistance

Strains of P. falciparum with decreased susceptibility to atovaquone or proguanil/cycloguanil alone can be selected in vitro or in vivo. The combination of atovaquone and proguanil hydrochloride may not be effective for treatment of recrudescent malaria that develops after prior therapy with the combination.

13 NONCLINICAL TOXICOLOGY

13.1 Carcinogenesis, Mutagenesis, Impairment of Fertility

Genotoxicity studies have not been performed with atovaquone in combination with proguanil. Effects of MALARONE on male and female reproductive performance are unknown.

Atovaquone

A 24‑month carcinogenicity study in CD rats was negative for neoplasms at doses up to 500 mg/kg/day corresponding to approximately 54 times the average steady‑state plasma concentrations in humans during prophylaxis of malaria. In CD-1 mice, a 24‑month study showed treatment‑related increases in incidence of hepatocellular adenoma and hepatocellular carcinoma at all doses tested (50, 100, and 200 mg/kg/day) which correlated with at least 15 times the average steady‑state plasma concentrations in humans during prophylaxis of malaria.

Atovaquone was negative with or without metabolic activation in the Ames Salmonella mutagenicity assay, the mouse lymphoma mutagenesis assay, and the cultured human lymphocyte cytogenetic assay. No evidence of genotoxicity was observed in the in vivo mouse micronucleus assay.

Atovaquone administered by oral gavage in doses of 100, 300, or 1,000 mg/kg/day to adult male rats from 73 days prior to mating until 20 days after mating and to adult female rats from 14 days prior to mating until LD20 did not impair male or female fertility or early embryonic development at doses up to 1,000 mg/kg/day corresponding to plasma exposures of approximately 7.3 times the estimated human exposure for the treatment of malaria based on AUC.

Proguanil

No evidence of a carcinogenic effect was observed in 24‑month studies conducted in CD-1 mice at doses up to 16 mg/kg/day corresponding to 1.5 times the average human plasma exposure during prophylaxis of malaria based on AUC, and in Wistar Hannover rats at doses up to 20 mg/kg/day corresponding to 1.1 times the average human plasma exposure during prophylaxis of malaria based on AUC.

Proguanil was negative with or without metabolic activation in the Ames Salmonella mutagenicity assay and the mouse lymphoma mutagenesis assay. No evidence of genotoxicity was observed in the in vivo mouse micronucleus assay.

Cycloguanil, the active metabolite of proguanil, was also negative in the Ames test, but was positive in the mouse lymphoma assay and the mouse micronucleus assay. These positive effects with cycloguanil, a dihydrofolate reductase inhibitor, were significantly reduced or abolished with folinic acid supplementation.

Proguanil administered orally in doses of 4, 8, and 16 mg/kg/day to male rats from 29 days prior to mating until 27 days after mating and to females from 15 days prior to mating through GD7 revealed no adverse effects on adult male or female fertility or early embryonic development at doses up to 16 mg/kg/day (up to 0.04 times the average human exposure for the treatment of malaria based on AUC). Fertility studies of proguanil in animals at exposures similar to or greater than those observed in humans have not been conducted.

13.2 Animal Toxicology and/or Pharmacology

Fibrovascular proliferation in the right atrium, pyelonephritis, bone marrow hypocellularity, lymphoid atrophy, and gastritis/enteritis were observed in dogs treated with proguanil hydrochloride for 6 months at a dose of 12 mg/kg/day (approximately 3.9 times the recommended daily human dose for malaria prophylaxis on a mg/m^2 basis). Bile duct hyperplasia, gall bladder mucosal atrophy, and interstitial pneumonia were observed in dogs treated with proguanil hydrochloride for 6 months at a dose of 4 mg/kg/day (approximately 1.3 times the recommended daily human dose for malaria prophylaxis on a mg/m^2 basis). Mucosal hyperplasia of the cecum and renal tubular basophilia were observed in rats treated with proguanil hydrochloride for 6 months at a dose of 20 mg/kg/day (approximately 1.6 times the recommended daily human dose for malaria prophylaxis on a mg/m^2 basis). Adverse heart, lung, liver, and gall bladder effects observed in dogs and kidney effects observed in rats were not shown to be reversible.

14 CLINICAL STUDIES

14.1 Prevention of P. falciparum Malaria

MALARONE was evaluated for prophylaxis of P. falciparum malaria in 5 clinical trials in malaria‑endemic areas and in 3 active‑controlled trials in non‑immune travelers to malaria‑endemic areas.

Three placebo‑controlled trials of 10 to 12 weeks’ duration were conducted among residents of malaria‑endemic areas in Kenya, Zambia, and Gabon. The mean age of subjects was 30 (range: 17 to 55), 32 (range: 16 to 64), and 10 (range: 5 to 16) years, respectively. Of a total of 669 randomized patients (including 264 pediatric patients aged 5 to 16 years), 103 were withdrawn for reasons other than falciparum malaria- or drug‑related adverse events (55% of these were lost to follow‑up and 45% were withdrawn for protocol violations). The results are listed in Table 6.

Table 6. Prevention of Parasitemiaa in PlaceboControlled Clinical Trials of MALARONE for Prophylaxis of P. falciparum Malaria in Residents of MalariaEndemic Areas
 | MALARONE | Placebo
Total number of patients randomized | 326 | 343
Failed to complete study | 57 | 46
Developed parasitemia (P. falciparum) | 2 | 92
a Free of parasitemia during the 10- to 12-week period of prophylactic therapy.

In another study, 330 Gabonese pediatric patients (weighing 13 to 40 kg and aged 4 to 14 years) who had received successful open‑label radical cure treatment with artesunate, were randomized to receive either MALARONE (dosage based on body weight) or placebo in a double‑blind fashion for 12 weeks. Blood smears were obtained weekly and any time malaria was suspected. Nineteen of the 165 children given MALARONE and 18 of 165 patients given placebo withdrew from the study for reasons other than parasitemia (primary reason was lost to follow-up). One out of 150 evaluable patients (<1%) who received MALARONE developed P. falciparum parasitemia while receiving prophylaxis with MALARONE compared with 31 (22%) of the 144 evaluable placebo recipients.

In a 10‑week study in 175 South African subjects who moved into malaria‑endemic areas and were given prophylaxis with 1 MALARONE tablet daily, parasitemia developed in 1 subject who missed several doses of medication. Since no placebo control was included, the incidence of malaria in this study was not known.

Two active-controlled trials were conducted in non‑immune travelers who visited a malaria‑endemic area. The mean duration of travel was 18 days (range: 2 to 38 days). Of a total of 1,998 randomized patients who received MALARONE or controlled drug, 24 discontinued from the study before follow-up evaluation 60 days after leaving the endemic area. Nine of these were lost to follow-up, 2 withdrew because of an adverse experience, and 13 were discontinued for other reasons. These trials were not large enough to allow for statements of comparative efficacy. In addition, the true exposure rate to P. falciparum malaria in both trials is unknown. The results are listed in Table 7.

Table 7. Prevention of Parasitemiaa in ActiveControlled Clinical Trials of MALARONE for Prophylaxis of P. falciparum Malaria in Non-Immune Travelers
 | MALARONE | Mefloquine | Chloroquine plus Proguanil
Total number of randomized patients who received study drug | 1,004 | 483 | 511
Failed to complete study | 14 | 6 | 4
Developed parasitemia (P. falciparum) | 0 | 0 | 3
a Free of parasitemia during the period of prophylactic therapy.

A third randomized, open‑label study was conducted which included 221 otherwise healthy pediatric patients (weighing ≥11 kg and aged 2 to 17 years) who were at risk of contracting malaria by traveling to an endemic area. The mean duration of travel was 15 days (range: 1 to 30 days). Prophylaxis with MALARONE (n = 110, dosage based on body weight) began 1 or 2 days before entering the endemic area and lasted until 7 days after leaving the area. A control group (n = 111) received prophylaxis with chloroquine/proguanil dosed according to WHO guidelines. No cases of malaria occurred in either group of children. However, the study was not large enough to allow for statements of comparative efficacy. In addition, the true exposure rate to P. falciparum malaria in this study is unknown.

Causal Prophylaxis

In separate trials with small numbers of volunteers, atovaquone and proguanil hydrochloride were independently shown to have causal prophylactic activity directed against liver‑stage parasites of P. falciparum. Six patients given a single dose of atovaquone 250 mg 24 hours prior to malaria challenge were protected from developing malaria, whereas all 4 placebo‑treated patients developed malaria.

During the 4 weeks following cessation of prophylaxis in clinical trial participants who remained in malaria‑endemic areas and were available for evaluation, malaria developed in 24 of 211 (11.4%) subjects who took placebo and 9 of 328 (2.7%) who took MALARONE. While new infections could not be distinguished from recrudescent infections, all but 1 of the infections in patients treated with MALARONE occurred more than 15 days after stopping therapy. The single case occurring on Day 8 following cessation of therapy with MALARONE probably represents a failure of prophylaxis with MALARONE.

The possibility that delayed cases of P. falciparum malaria may occur sometime after stopping prophylaxis with MALARONE cannot be ruled out. Hence, returning travelers developing febrile illnesses should be investigated for malaria.

14.2 Treatment of Acute, Uncomplicated P. falciparum Malaria Infections

In 3 Phase 2 clinical trials, atovaquone alone, proguanil hydrochloride alone, and the combination of atovaquone and proguanil hydrochloride were evaluated for the treatment of acute, uncomplicated malaria caused by P. falciparum. Among 156 evaluable patients, the parasitological cure rate (elimination of parasitemia with no recurrent parasitemia during follow‑up for 28 days) was 59/89 (66%) with atovaquone alone, 1/17 (6%) with proguanil hydrochloride alone, and 50/50 (100%) with the combination of atovaquone and proguanil hydrochloride.

MALARONE was evaluated for treatment of acute, uncomplicated malaria caused by P. falciparum in 8 Phase 3 randomized, open-label, controlled clinical trials (N = 1,030 enrolled in both treatment groups). The mean age of subjects was 27 years and 16% were children 12 years and younger; 74% of subjects were male. Evaluable patients included those whose outcomes at 28 days were known. Among 471 evaluable patients treated with the equivalent of 4 MALARONE tablets once daily for 3 days, 464 had a sensitive response (elimination of parasitemia with no recurrent parasitemia during follow‑up for 28 days) (Table 8). Seven patients had a response of RI resistance (elimination of parasitemia but with recurrent parasitemia between 7 and 28 days after starting treatment). In these trials, the response to treatment with MALARONE was similar to treatment with the comparator drug in 4 trials.

Table 8. Parasitological Response in 8 Clinical Trials of MALARONE for Treatment of P. falciparum Malaria
Study Site | MALARONEa |  | Comparator
Study Site | Evaluable Patients; (n) | % Sensitive; Responseb | Drug(s) | Evaluable Patients; (n) | % Sensitive Responseb
Brazil | 74 | 98.6% | Quinine and tetracycline | 76 | 100.0%
Thailand | 79 | 100.0% | Mefloquine | 79 | 86.1%
Francec | 21 | 100.0% | Halofantrine | 18 | 100.0%
Kenyac,d | 81 | 93.8% | Halofantrine | 83 | 90.4%
Zambia | 80 | 100.0% | Pyrimethamine/; sulfadoxine (P/S) | 80 | 98.8%
Gabonc | 63 | 98.4% | Amodiaquine | 63 | 81.0%
Philippines | 54 | 100.0% | Chloroquine (Cq); Cq and P/S | 23; 32 | 30.4%; 87.5%
Peru | 19 | 100.0% | Chloroquine; P/S | 13; 7 | 7.7%; 100.0%
a MALARONE = 1,000 mg atovaquone and 400 mg proguanil hydrochloride (or equivalent based on body weight for patients weighing ≤40 kg) once daily for 3 days.
b Elimination of parasitemia with no recurrent parasitemia during follow‑up for 28 days.
c Patients hospitalized only for acute care. Follow‑up conducted in outpatients.
d Study in pediatric patients aged 3 to 12 years.

When these 8 trials were pooled and 2 additional trials evaluating MALARONE alone (without a comparator arm) were added to the analysis, the overall efficacy (elimination of parasitemia with no recurrent parasitemia during follow‑up for 28 days) in 521 evaluable patients was 98.7%.

The efficacy of MALARONE in the treatment of the erythrocytic phase of non-falciparum malaria was assessed in a small number of patients. Of the 23 patients in Thailand infected with P. vivax and treated with atovaquone/proguanil hydrochloride 1,000 mg/400 mg daily for 3 days, parasitemia cleared in 21 (91.3%) at 7 days. Parasite relapse occurred commonly when P. vivax malaria was treated with MALARONE alone. Relapsing malarias including P. vivax and P. ovale require additional treatment to prevent relapse.

The efficacy of MALARONE in treating acute uncomplicated P. falciparum malaria in children weighing ≥5 and <11 kg was examined in an open‑label, randomized trial conducted in Gabon. Patients received either MALARONE (2 or 3 MALARONE pediatric tablets once daily depending upon body weight) for 3 days (n = 100) or amodiaquine (10 mg/kg/day) for 3 days (n = 100). In this study, the MALARONE tablets were crushed and mixed with condensed milk just prior to administration. An adequate clinical response (elimination of parasitemia with no recurrent parasitemia during follow‑up for 28 days) was obtained in 95% (87/92) of the evaluable pediatric patients who received MALARONE and in 53% (41/78) of those evaluable who received amodiaquine. A response of RI resistance (elimination of parasitemia but with recurrent parasitemia between 7 and 28 days after starting treatment) was noted in 3% and 40% of the patients, respectively. Two cases of RIII resistance (rising parasite count despite therapy) were reported in the patients receiving MALARONE. There were 4 cases of RIII in the amodiaquine arm.

16 HOW SUPPLIED/STORAGE AND HANDLING

MALARONE tablets, containing 250 mg atovaquone and 100 mg proguanil hydrochloride.

- Bottle of 100 tablets with child-resistant closure (NDC 0173-0675-01).
- Unit Dose Pack of 24 tablets with child-resistant lid foil (NDC 0173-0675-02).

MALARONE pediatric tablets, containing 62.5 mg atovaquone and 25 mg proguanil hydrochloride.

- Bottle of 100 tablets with child-resistant closure (NDC 0173-0676-01).

Storage Conditions

Store at 25°C (77°F). Temperature excursions are permitted to 15° to 30°C (59° to 86°F) (see USP Controlled Room Temperature).

17 PATIENT COUNSELING INFORMATION

Patients should be instructed:

- to take MALARONE at the same time each day with food or a milky drink.
- to take a repeat dose of MALARONE if vomiting occurs within 1 hour after dosing.
- to take a dose as soon as possible if a dose is missed, then return to their normal dosing schedule. However, if a dose is skipped, the patient should not double the next dose.
- that rare serious adverse events such as hepatitis, severe skin reactions, neurological events, and hematological events have been reported when MALARONE was used for the prophylaxis or treatment of malaria.
- to consult a healthcare professional regarding alternative forms of prophylaxis if prophylaxis with MALARONE is prematurely discontinued for any reason.
- that protective clothing, insect repellents, and bed nets are important components of malaria prophylaxis.
- that no chemoprophylactic regimen is 100% effective; therefore, patients should seek medical attention for any febrile illness that occurs during or after return from a malaria‑endemic area and inform their healthcare professional that they may have been exposed to malaria.
- that falciparum malaria carries a higher risk of death and serious complications in pregnant women than in the general population. Pregnant women anticipating travel to malarious areas should discuss the risks and benefits of such travel with their physicians.

Trademark is owned by or licensed to the GSK group of companies.

Distributed by:

GlaxoSmithKline

Durham, NC 27701

©2023 GSK group of companies or its licensor.

MLR:11PI

PACKAGE LABEL

PRINCIPAL DISPLAY PANEL

NDC 0173-0675-01

MALARONE

(atovaquone and proguanil HCl)

Tablets

Each tablet contains 250 mg atovaquone and 100 mg proguanil HCl.

Rx only

GSK

100 Tablets

See accompanying prescribing information for Dosage and Administration.

Store at 25oC (77oF); excursions permitted to 15o to 30oC (59o to 86oF) (see USP Controlled Room Temperature).

Do not use if printed safety seal under cap is broken or missing.

Trademarks owned or licensed by GSK.

Distributed by:

GlaxoSmithKline

Durham, NC 27701

Made in Canada

©2024 GSK or licensor.

Rev. 01/24

A091927 (62000000091927)

PACKAGE LABEL

PRINCIPAL DISPLAY PANEL

NDC 0173-0676-01

MALARONE

(atovaquone and proguanil HCl)

Pediatric Tablets

Each tablet contains 62.5 mg atovaquone and 25 mg proguanil HCl.

Rx only

GSK

100 Tablets

See accompanying prescribing information for Dosage and Administration.

Store at 25oC (77oF); excursions permitted to 15o to 30oC (59o to 86oF) (see USP Controlled Room Temperature).

Do not use if printed safety seal under cap is broken or missing.

Trademarks owned or licensed by GSK.

Distributed by:

GlaxoSmithKline

Durham, NC 27701

Made in Canada

©2023 GSK or licensor.

Rev. 01/24

A091928 (62000000091928)